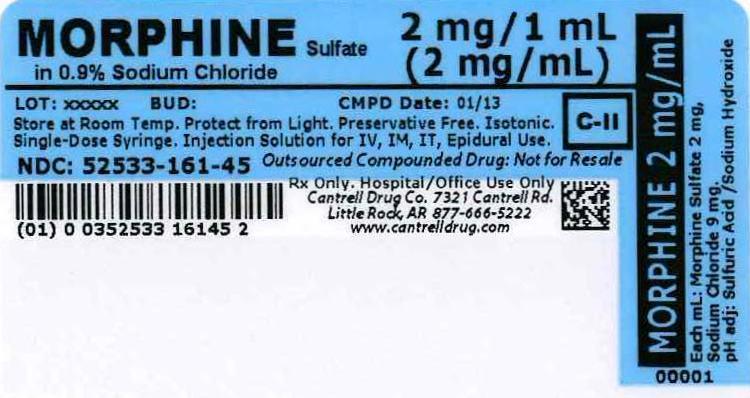 DRUG LABEL: Morphine Sulfate
NDC: 52533-161 | Form: INJECTION, SOLUTION
Manufacturer: Cantrell Drug Company
Category: prescription | Type: HUMAN PRESCRIPTION DRUG LABEL
Date: 20140502
DEA Schedule: CII

ACTIVE INGREDIENTS: Morphine Sulfate 2 mg/1 mL
INACTIVE INGREDIENTS: Sodium Chloride 9 mg/1 mL; Water

Morphine Sulfate 2 mg/mL in 0.9% Sodium Chloride Syringe